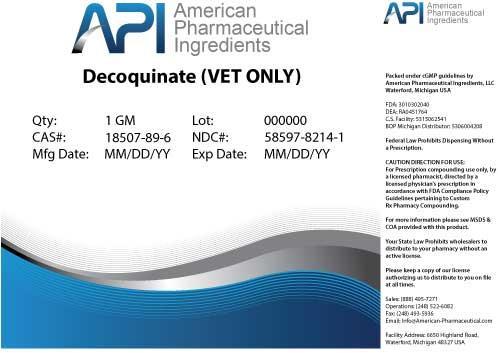 DRUG LABEL: Decoquinate
NDC: 58597-8214 | Form: POWDER
Manufacturer: AMERICAN PHARMACEUTICAL INGREDIENTS LLC
Category: other | Type: BULK INGREDIENT
Date: 20140425

ACTIVE INGREDIENTS: Decoquinate 1 g/1 g

Decoquinate